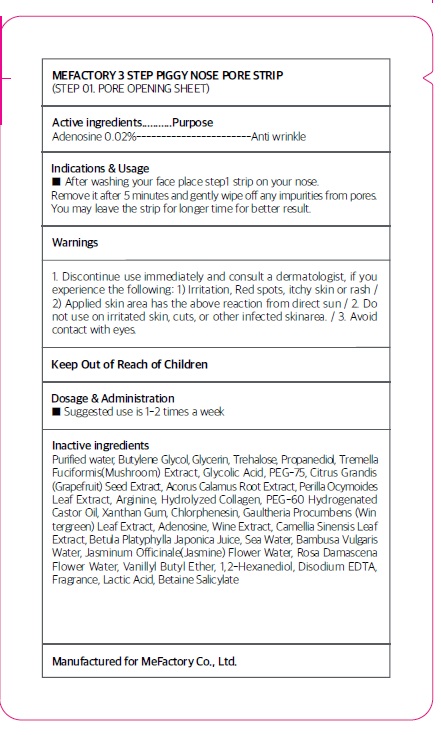 DRUG LABEL: Mefactory 3Step Piggy Nose Pore Strip Step 01 Pore Opening Sheet
NDC: 70908-080 | Form: PATCH
Manufacturer: MeFactory Co., Ltd.
Category: otc | Type: HUMAN OTC DRUG LABEL
Date: 20170303

ACTIVE INGREDIENTS: Adenosine 0.6 mg/3 g
INACTIVE INGREDIENTS: WATER; Butylene Glycol

ACTIVE INGREDIENT

Active ingredients: Adenosine 0.02%

INACTIVE INGREDIENT

Inactive ingredients: Purified water,Butylene Glycol,Glycerin,Trehalose ,Propanediol,Tremella Fuciformis (Mushroom) Extract,Glycolic Acid ,PEG-75 ,Citrus Grandis (Grapefruit) Seed Extract ,Acorus Calamus Root Extract,Perilla Ocymoides Leaf Extract ,Arginine,Hydrolyzed Collagen ,PEG-60 Hydrogenated Castor Oil ,Xanthan Gum ,Chlorphenesin ,Gaultheria Procumbens (Wintergreen) Leaf Extract,Adenosine ,Wine Extract ,Camellia Sinensis Leaf Extract ,Betula Platyphylla Japonica Juice ,Sea Water,Bambusa Vulgaris Water,Jasminum Officinale (Jasmine) Flower Water ,Rosa Damascena Flower Water ,Vanillyl Butyl Ether,1,2-Hexanediol ,Disodium EDTA ,Fragrance,Lactic Acid ,Betaine Salicylate

PURPOSE

Purpose: Anti wrinkle

WARNINGS

Warnings: 1. Discontinue use immediately and consult a dermatologist, if you experience the following: 1) Irritation, Red spots, itchy skin or rash 2) Applied skin area has the above reaction from direct sun 2. Do not use on irritated skin, cuts, or other infected skin area. 3. Avoid contact with eyes.

KEEP OUT OF REACH OF CHILDREN

INDICATIONS & USAGE

Indications & Usage: After washing your face place step1 strip on your nose. Remove it after 5 minutes and gently wipe off any impurities from pores. You may leave the strip for longer time for better result.

DOSAGE & ADMINISTRATION

Dosage & Administration: Suggested use is 1-2 times a week